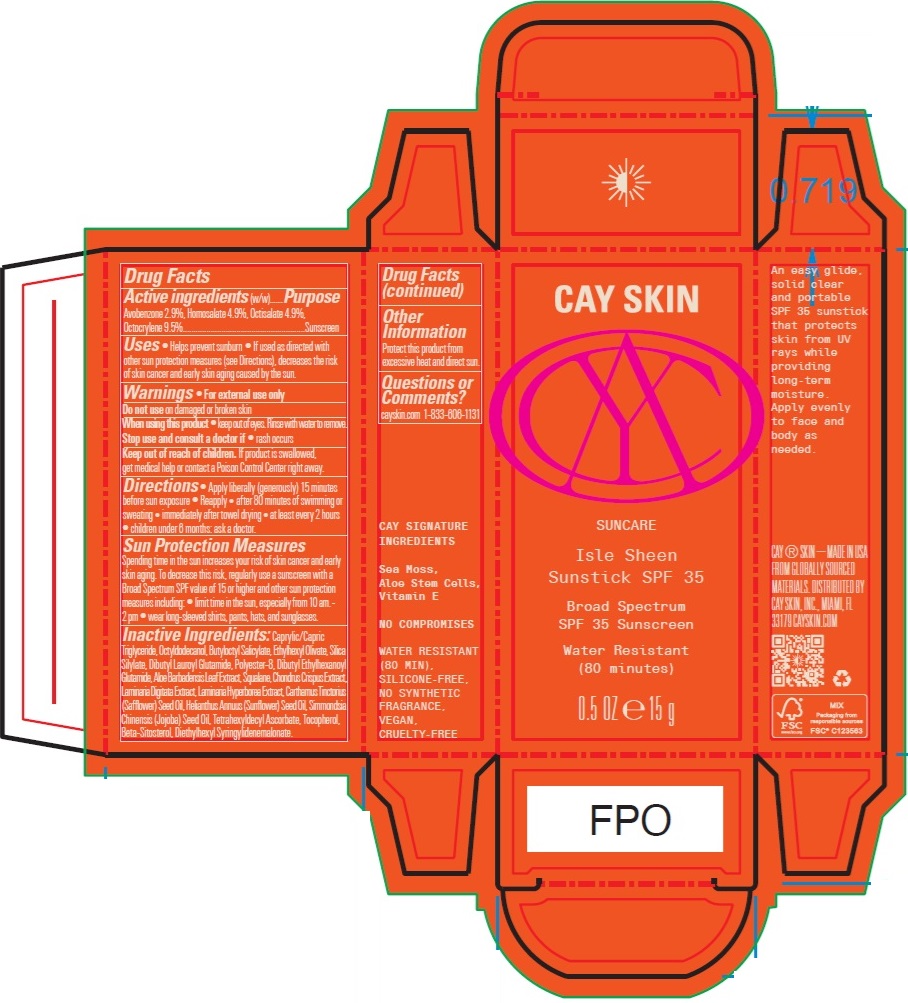 DRUG LABEL: Cay Skin Isle Sheen Sunstick SPF 35
NDC: 82657-007 | Form: STICK
Manufacturer: Cay Skin, Inc.
Category: otc | Type: HUMAN OTC DRUG LABEL
Date: 20241205

ACTIVE INGREDIENTS: OCTISALATE 49 mg/1 g; AVOBENZONE 29 mg/1 g; HOMOSALATE 49 mg/1 g; OCTOCRYLENE 95 mg/1 g
INACTIVE INGREDIENTS: ETHYLHEXYL OLIVATE; SQUALANE; CAPRYLIC/CAPRIC TRIGLYCERIDE; BUTYLOCTYL SALICYLATE; CHONDRUS CRISPUS; SAFFLOWER OIL; JOJOBA OIL; TETRAHEXYLDECYL ASCORBATE; TOCOPHEROL; LAMINARIA DIGITATA EXTRACT; LAMINARIA HYPERBOREA EXTRACT; SUNFLOWER OIL; OCTYLDODECANOL; DIBUTYL LAUROYL GLUTAMIDE; DIBUTYL ETHYLHEXANOYL GLUTAMIDE; ALOE VERA LEAF; BETA-SITOSTEROL; DIETHYLHEXYL SYRINGYLIDENEMALONATE

Cay Skin Isle Sheen Sunstick SPF 35

Active ingredients

Avobenzone 2.9%

Homosalate 4.9%

Octisalate 4.9%

Octocrylene 9.5%

Purpose

Sunscreen

Uses

- Helps prevent sunburn
- If used as directed with other sun protection measures (see Directions), decreases the risk of skin cancer and early skin aging caused by the sun.

Warnings

For external use only

Do not use

on damaged or broken skin

When using this product

- keep out of eyes. Rinse with water to remove.

Stop use and consult a doctor if

- rash occurs

Keep out of reach of children.

If product is swallowed, get medical help or contact a Poison Control Center right away.

Directions

- Apply liberally (generously) 15 minutes before sun exposure
- Reapply
- after 80 minutes of swimming or sweating
- immediately after towel drying
- at least every 2 hours
- children under 6 months: ask a doctor

Sun Protection Measures. Spending time in the sun increases your risk of skin cancer and early skin aging. To decrease this risk, regularly use a sunscreen with a Broad Spectrum SPF value of 15 or higher and other sun protection measures including:

- limit time in the sun, especially from 10 am. - 2 pm
- wear long-sleeved shirts, pants, hats, and sunglasses

Inactive Ingredients

Caprylic/Capric Triglyceride, Octyldodecanol, Butyloctyl Salicylate, Ethylhexyl Olivate, Silica Silylate, Dibutyl Lauroyl Glutamide, Polyester-8, Dibutyl Ethylhexanoyl Glutamide, Aloe Barbadensis Leaf Extract, Squalane, Chondrus Crispus Extract, Laminaria Digitata Extract, Laminaria Hyperborea Extract, Carthamus Tinctorius (Safflower) Seed Oil, Helianthus Annuus (Sunflower) Seed Oil, Simmondsia Chinensis (Jojoba) Seed Oil, Tetrahexyldecyl Ascorbate, Tocopherol, Beta-Sitosterol, Diethylhexyl Syringylidenemalonate.

Other Information

Protect this product from excessive heat and direct sun.

Questions or Comments?

cayskin.com 1-833-606-1131

Company Information

Distributed by Cay Skin, Inc., Miami, FL 33179

cayskin.com